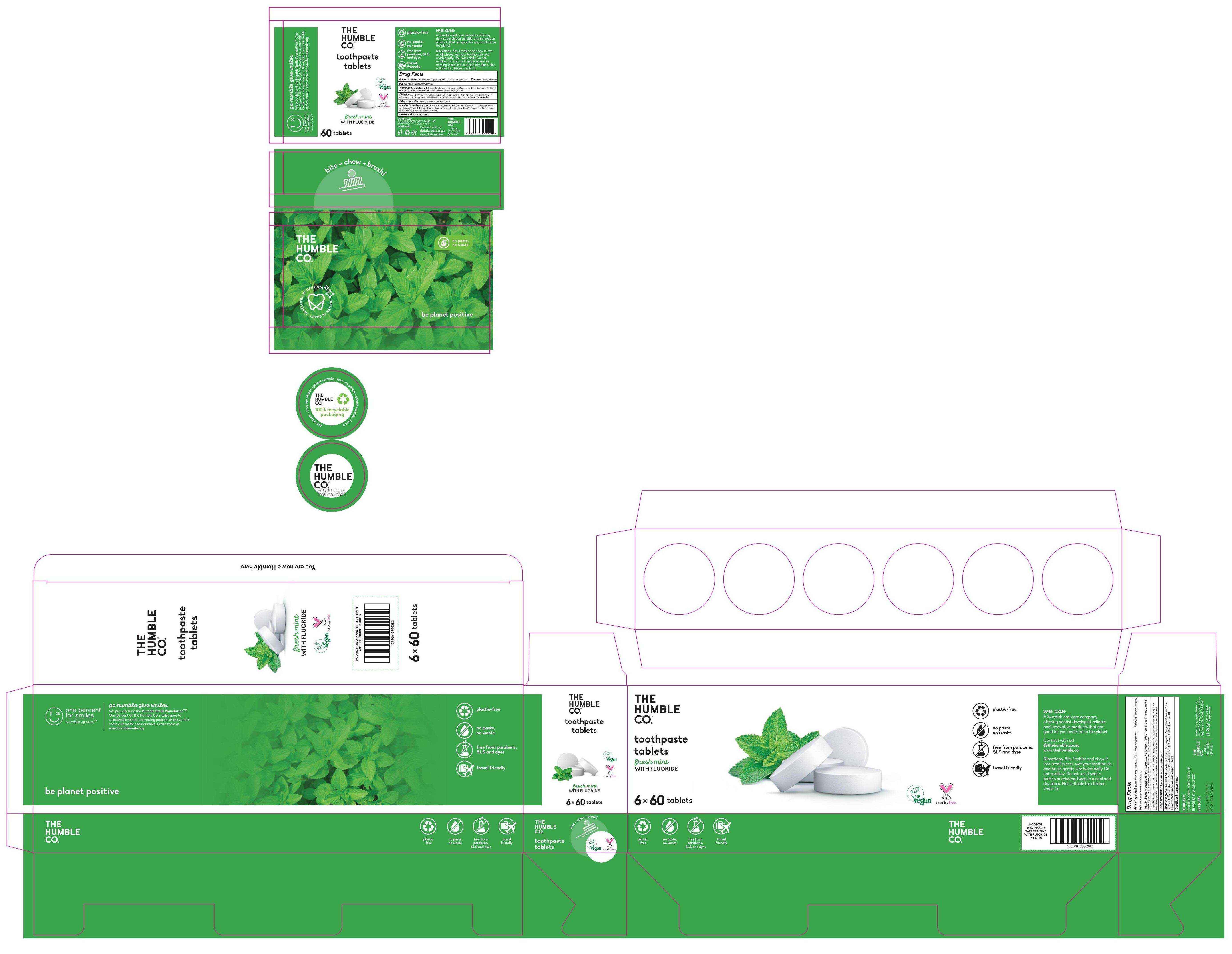 DRUG LABEL: Tooth
NDC: 83861-001 | Form: TABLET
Manufacturer: Henan Dailygreen Biotechnology Co. LTD
Category: otc | Type: HUMAN OTC DRUG LABEL
Date: 20231211

ACTIVE INGREDIENTS: SODIUM MONOFLUOROPHOSPHATE 0.877 g/100 1
INACTIVE INGREDIENTS: STEVIA REBAUDIANA WHOLE; PEPPERMINT OIL; CITRUS AURANTIUM FLOWER OIL; MAGNESIUM STEARATE; CALCIUM CARBONATE; XYLITOL; COCAMIDOPROPYL BETAINE; SORBITOL; MENTHA SPICATA OIL

83861-001

Active ingredient

sodium monofluorophosphate 0.877% (1100ppm w/v fluoride ion)

Purpose

Anticavity Toothpaste

Use

aids in the prevention of dental cavities

Warnings

Keep out of reach of children Not to be used by children under 12 years of age. If more than used for brushing isaccidentally swallowed get medical help or contact a Poison Control Center right away.

DO NOT USE

Not to be used by children under 12 years of age .

WHEN USING

n/a

STOP USE

n/a

Keep out of reach of children

Directions

Adults : Wet your toothbrush and crush the tab between your teeth Brush like normal. Rinse after using . Brushteeth thoroughly preferably after each meal or at least twice a day or as directed by a dentist or physician. Do not swallow

Other Information

Store at room temperature and dry place.

Inactive ingredients

Sorbitol , Calcium Carbonate , Probiotics , Xylitol , Magnesium Stearate , Stevia Rebaudiana Extract ,Tea (Camellia Sinensis) Polyphenols , Peppermint (Mentha Piperita) oil , Bitter Orange (Citrus Aurantium) Flower Oil , Peppermint (Mentha Piperita) Leaf oil , Cocamidopropyl Betaine